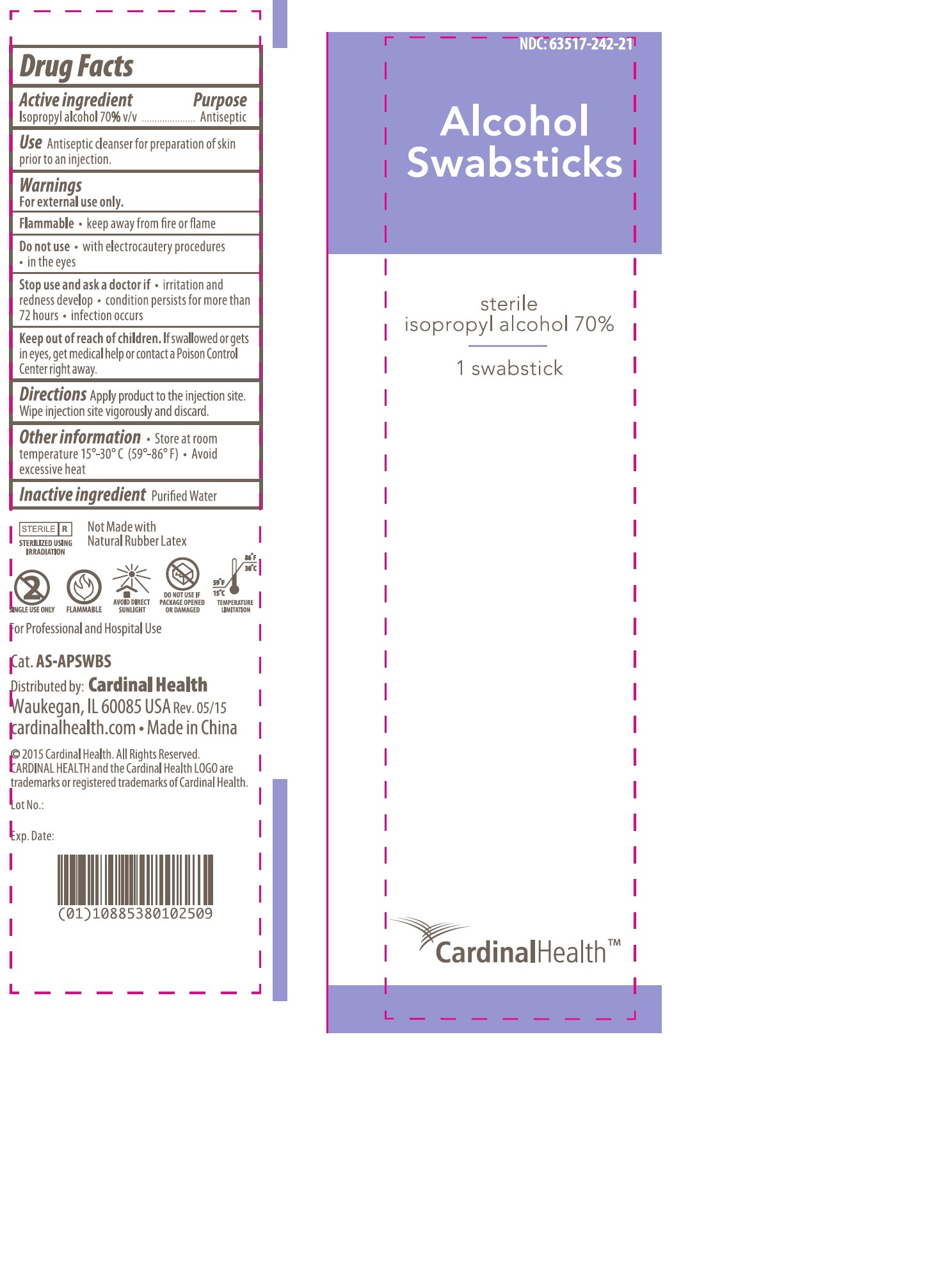 DRUG LABEL: Alcohol sterile
NDC: 63517-242 | Form: SWAB
Manufacturer: Cardinal Health, Inc
Category: otc | Type: HUMAN OTC DRUG LABEL
Date: 20241121

ACTIVE INGREDIENTS: ISOPROPYL ALCOHOL 0.7 mL/1 mL
INACTIVE INGREDIENTS: WATER

Alcohol Swabsticks sterile, 1 per pouch, 50 pouches/box

Active ingredient

Isopropyl alcohol 70% v/v

Purpose

Antiseptic

Use

Antiseptic cleanser for preparation of skin prior to an injection

Warnings

For external use only.

Flammable

- keep away from fire or flame

Do not use

- with eletrocautery procedures
- in the eyes

Stop use and ask a doctor if

- irritation and redness develop
- condition persists for more than 72 hours
- infection occurs

Keep out of reach of children.

If swallowed or gets in eyes, get medical help or contact a Poison Control Center right away.

Directions

Apply product to the injection site. Wipe injection site vigorously and discard

Other information

- Store at room temperature 15° - 30° C (59° -86° F)
- Avoid excessive heat

Inactive ingredient

Purified water